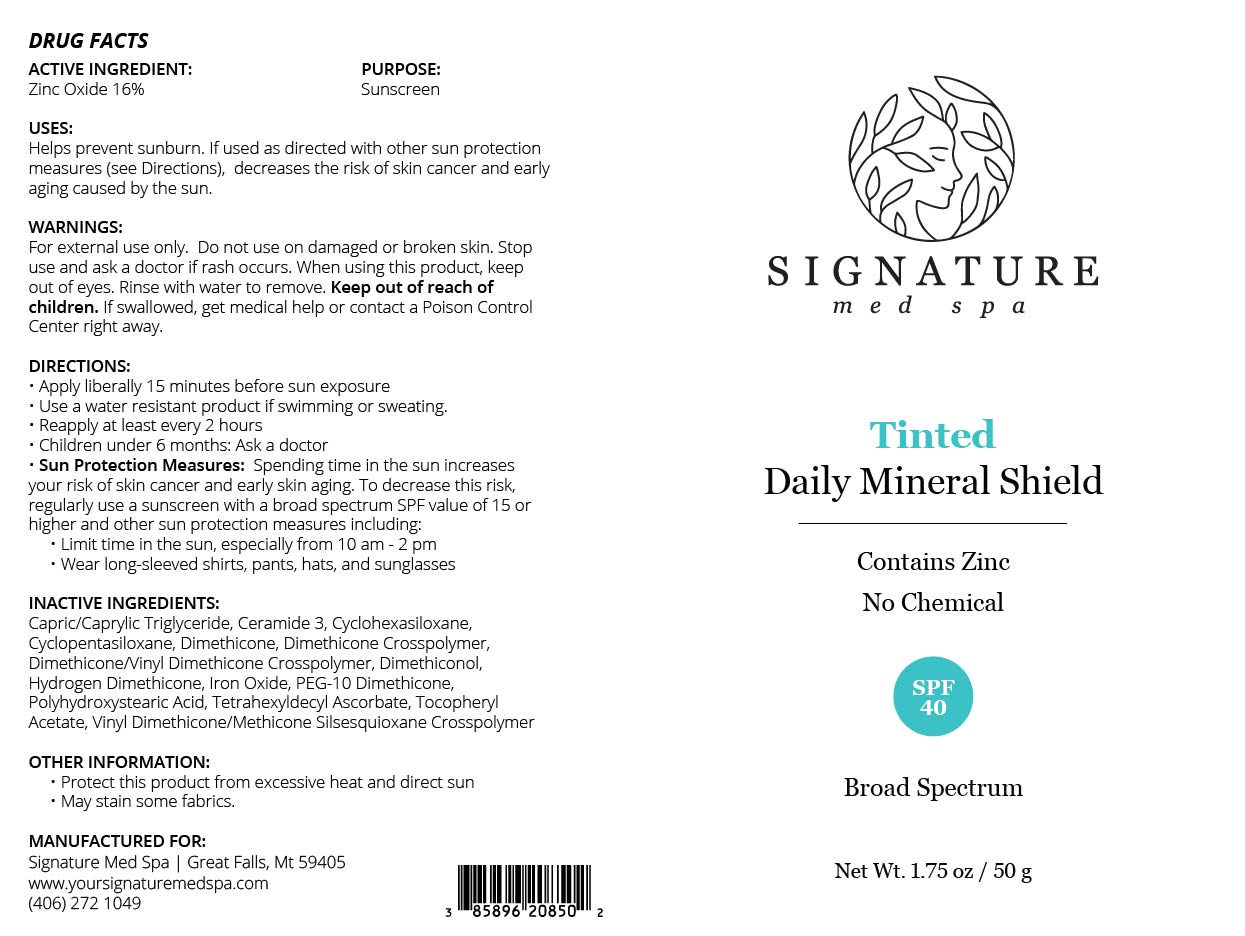 DRUG LABEL: Tinted Daily Mineral Shield
NDC: 85896-208 | Form: CREAM
Manufacturer: SIGNATURE MED SPA MT LLC
Category: otc | Type: HUMAN OTC DRUG LABEL
Date: 20251217

ACTIVE INGREDIENTS: ZINC OXIDE 160 mg/1 g
INACTIVE INGREDIENTS: HYDROGEN DIMETHICONE (20 CST); DIMETHICONE/VINYL DIMETHICONE CROSSPOLYMER (SOFT PARTICLE); ALPHA-TOCOPHEROL ACETATE; TETRAHEXYLDECYL ASCORBATE; POLYHYDROXYSTEARIC ACID (2300 MW); CERAMIDE 3; CYCLOPENTASILOXANE; CYCLOHEXASILOXANE; VINYL DIMETHICONE/METHICONE SILSESQUIOXANE CROSSPOLYMER; CAPRYLIC/CAPRIC TRIGLYCERIDE; CI 77491; CI 77492; DIMETHICONE; DIMETHICONOL (2000 CST); CI 77499; DIMETHICONE CROSSPOLYMER; PEG-10 DIMETHICONE (600 CST)

ACTIVE INGREDIENT(S)

Zinc Oxide 16%

PURPOSE

SUNSCREEN

USES:

Helps Prevent Sunburn. If used as directed with other sun protection measures (see “Directions”), decreases the risk of skin cancer and early skin aging caused by the sun.

WARNINGS

For external use only. Do not use on broken or damaged skin. Stop use and ask a doctor if rash occurs. When using this product, keep out of eyes. Rinse with water to remove. Keep out of reach of children. If swallowed, get medical help or contact a poison control center right away.

WARNING

KEEP OUT OF REACH OF CHILDREN

DIRECTIONS

Apply liberally 15 minutes before sun exposure. Use a water-resistant product if swimming or sweating. Reapply at least every 2 hours. Children under 6 months: Ask a doctor. Sun Protection Measures: Spending time in the sun increases your risk of skin cancer and early skin aging. To decrease this risk, regularly use a sunscreen with a Broad-Spectrum SPF value of 15 or higher and other sun protection measures including: Limit time in the sun, especially from 10 a.m. - 2 p.m. Wear long-sleeved shirts, pants, hats and sunglasses.

INACTIVE INGREDIENTS

Capric/Caprylic Triglyceride, Ceramide 3, Cyclohexasiloxane, Cyclopentasiloxane, Dimethicone, Dimethicone Crosspolymer, Dimethicone/Vinyl Dimethicone Crosspolymer, Dimethiconol, Iron Oxide, Hydrogen Dimethicone, PEG-10 Dimethicone, Polyhydroxystearic Acid, Tetrahexyldecyl Ascorbate, Tocopheryl Acetate, Vinyl Dimethicone/Methicone Silsesquioxane Crosspolymer

OTHER INFORMATION

Protect this product from excessive heat and direct sun

May stain some fabrics